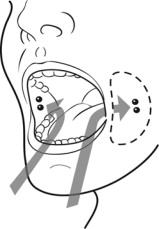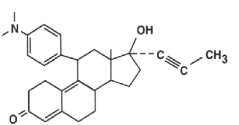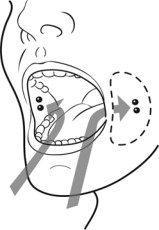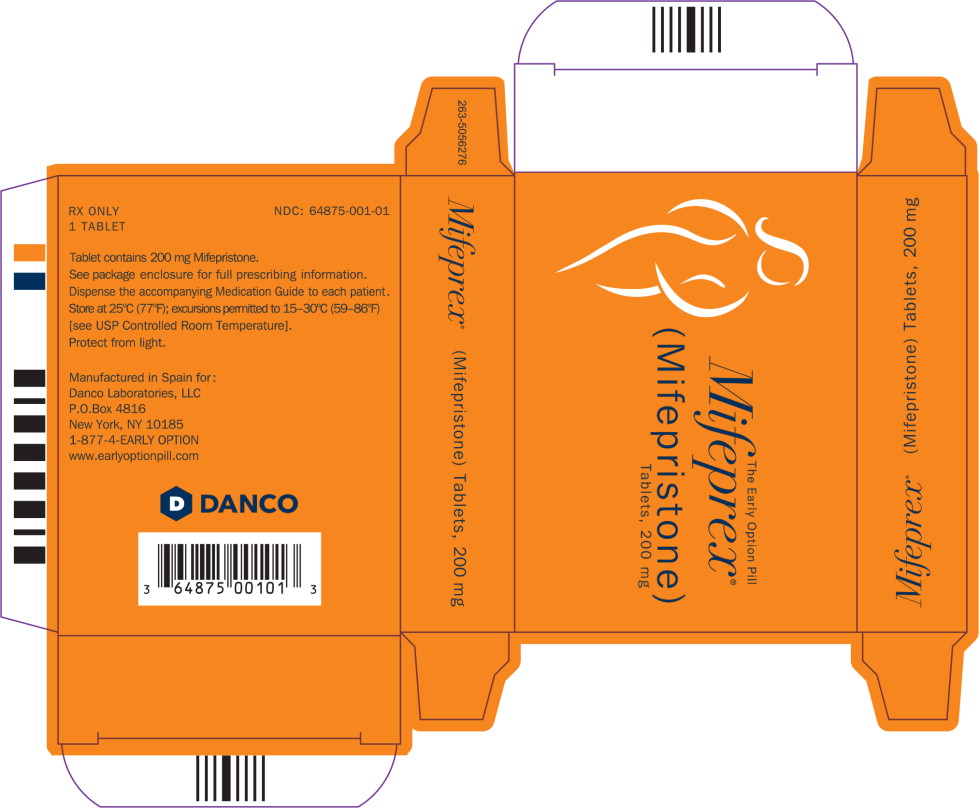 DRUG LABEL: MIFEPREX
NDC: 64875-001 | Form: TABLET
Manufacturer: Danco Laboratories, LLC
Category: prescription | Type: HUMAN PRESCRIPTION DRUG LABEL
Date: 20260107

ACTIVE INGREDIENTS: MIFEPRISTONE 200 mg/1 1
INACTIVE INGREDIENTS: SILICON DIOXIDE; STARCH, CORN; POVIDONE, UNSPECIFIED; MICROCRYSTALLINE CELLULOSE; MAGNESIUM STEARATE

HIGHLIGHTS OF PRESCRIBING INFORMATION

These highlights do not include all the information needed to use MIFEPREX safely and effectively. See full prescribing information for MIFEPREX.
MIFEPREX®(mifepristone) tablets, for oral use
Initial U.S. Approval: 2000

WARNING: SERIOUS AND SOMETIMES FATAL INFECTIONS OR BLEEDING

See full prescribing information for complete boxed warning.

Serious and sometimes fatal infections and bleeding occur very rarely following spontaneous, surgical, and medical abortions, including following MIFEPREX use.

- Atypical Presentation of Infection. Patients with serious bacterial infections and sepsis can present without fever, bacteremia or significant findings on pelvic examination. A high index of suspicion is needed to rule out serious infection and sepsis. (5.1)
- Bleeding. Prolonged heavy bleeding may be a sign of incomplete abortion or other complications and prompt medical or surgical intervention may be needed. (5.2)

MIFEPREX is only available through a restricted program called the Mifepristone REMS Program (5.3).

Before prescribing MIFEPREX, inform the patient about these risks. Ensure the patient knows whom to call and what to do if they experience sustained fever, severe abdominal pain, prolonged heavy bleeding, or syncope, or if they experience abdominal pain or discomfort or general malaise for more than 24 hours after taking misoprostol.

1 INDICATIONS AND USAGE

MIFEPREX is a progestin antagonist indicated, in a regimen with misoprostol, for the medical termination of intrauterine pregnancy through 70 days gestation. (1)

2 DOSAGE AND ADMINISTRATION

- 200 mg MIFEPREX on Day 1, followed 24-48 hours after MIFEPREX dosing by 800 mcg buccal misoprostol. (2.1)
- Instruct the patient what to do if significant adverse reactions occur. (2.2)
- Follow-up is needed to confirm complete termination of pregnancy. (2.3)

3 DOSAGE FORMS AND STRENGTHS

Tablets containing 200 mg of mifepristone each, supplied as 1 tablet on one blister card (3)

4 CONTRAINDICATIONS

- Confirmed/suspected ectopic pregnancy or undiagnosed adnexal mass (4)
- Chronic adrenal failure (4)
- Concurrent long-term corticosteroid therapy (4)
- History of allergy to mifepristone, misoprostol, or other prostaglandins (4)
- Hemorrhagic disorders or concurrent anticoagulant therapy (4)
- Inherited porphyria (4)
- Intrauterine device (IUD) in place (4)

5 WARNINGS AND PRECAUTIONS

- Ectopic pregnancy: Exclude before treatment. (5.4)
- Rhesus immunization: Prevention needed as for surgical abortion. (5.5)

6 Adverse Reactions

Most common adverse reactions (>15%) are nausea, weakness, fever/chills, vomiting, headache, diarrhea, and dizziness. (6)

To report SUSPECTED ADVERSE REACTIONS, contact Danco Laboratories, LLC at 1-877-432-7596 or medicaldirector@earlyoptionpill.com or FDA at 1-800-FDA-1088 orwww.fda.gov/medwatch.

7 DRUG INTERACTIONS

- CYP3A4 inducers can lower mifepristone concentrations. (7.1)
- CYP3A4 inhibitors can increase mifepristone concentrations. Use with caution. (7.2)
- CYP3A4 substrate concentrations can be increased. Caution with coadministration of substrates with narrow therapeutic margin. (7.3)

8 USE IN SPECIFIC POPULATIONS

- Pregnancy: Risk of fetal malformations in ongoing pregnancy if not terminated is unknown. (8.1)

FULL PRESCRIBING INFORMATION

WARNING: SERIOUS AND SOMETIMES FATAL INFECTIONS OR BLEEDING

Serious and sometimes fatal infections and bleeding occur very rarely following spontaneous, surgical, and medical abortions, including following MIFEPREX use. No causal relationship between the use of MIFEPREX and misoprostol and these events has been established.

- Atypical Presentation of Infection. Patients with serious bacterial infections (e.g., Clostridium sordellii) and sepsis can present without fever, bacteremia, or significant findings on pelvic examination following an abortion. Very rarely, deaths have been reported in patients who presented without fever, with or without abdominal pain, but with leukocytosis with a marked left shift, tachycardia, hemoconcentration, and general malaise. A high index of suspicion is needed to rule out serious infection and sepsis [see Warnings and Precautions (5.1)] .
- Bleeding. Prolonged heavy bleeding may be a sign of incomplete abortion or other complications and prompt medical or surgical intervention may be needed. Advise patients to seek immediate medical attention if they experience prolonged heavy vaginal bleeding [see Warnings and Precautions (5.2)] .

Because of the risks of serious complications described above, MIFEPREX is available only through a restricted program under a Risk Evaluation and Mitigation Strategy (REMS) called the Mifepristone REMS Program [see Warnings and Precautions (5.3)] .

Before prescribing MIFEPREX, inform the patient about the risk of these serious events. Ensure that the patient knows whom to call and what to do, including going to an Emergency Room if none of the provided contacts are reachable, if they experience sustained fever, severe abdominal pain, prolonged heavy bleeding, or syncope, or if they experience abdominal pain or discomfort, or general malaise (including weakness, nausea, vomiting, or diarrhea) for more than 24 hours after taking misoprostol.

1 INDICATIONS AND USAGE

MIFEPREX is indicated, in a regimen with misoprostol, for the medical termination of intrauterine pregnancy through 70 days gestation.

2 DOSAGE AND ADMINISTRATION

2.1 Dosing Regimen

For purposes of this treatment, pregnancy is dated from the first day of the last menstrual period. The duration of pregnancy may be determined from menstrual history and clinical examination. Assess the pregnancy by ultrasonographic scan if the duration of pregnancy is uncertain or if ectopic pregnancy is suspected.

Remove any intrauterine device (“IUD”) before treatment with MIFEPREX begins [ see Contraindications (4) ].

The dosing regimen for MIFEPREX and misoprostol is:

- MIFEPREX 200 mg orally + misoprostol 800 mcg buccally
  - Day One:MIFEPREX Administration
    One 200 mg tablet of MIFEPREX is taken in a single oral dose.
  - Day Two or Three:Misoprostol Administration (minimum24-hour interval between MIFEPREX and misoprostol)
    Four 200 mcg tablets (total dose 800 mcg) of misoprostol are taken by the buccal route.
    Tell the patient to place two 200 mcg misoprostol tablets in each cheek pouch (the area between the cheek and gums) for 30 minutes and then swallow any remnants with water or another liquid (see Figure 1).
    Figure 1
    2 pills between cheek and gum on left side + 2 pills between cheek and gum on right side

Patients taking MIFEPREX must take misoprostol within 24 to 48 hours after taking MIFEPREX. The effectiveness of the regimen may be lower if misoprostol is administered less than 24 hours or more than 48 hours after mifepristone administration.

Because most women will expel the pregnancy within 2 to 24 hours of taking misoprostol [see Clinical Studies (14)] , discuss with the patient an appropriate location for them to be when taking the misoprostol, taking into account that expulsion could begin within 2 hours of administration.

2.2 Patient Management Following Misoprostol Administration

During the period immediately following the administration of misoprostol, the patient may need medication for cramps or gastrointestinal symptoms [see Adverse Reactions (6)].

Give the patient:

- Instructions on what to do if significant discomfort, excessive vaginal bleeding or other adverse reactions occur
- A phone number to call if the patient has questions following the administration of the misoprostol
- The name and phone number of the healthcare provider who will be handling emergencies.

2.3 Post-treatment Assessment: Day 7 to 14

Patients should follow-up with their healthcare provider approximately 7 to 14 days after the administration of MIFEPREX. This assessment is very important to confirm that complete termination of pregnancy has occurred and to evaluate the degree of bleeding. Termination can be confirmed by medical history, clinical examination, human Chorionic Gonadotropin (hCG) testing, or ultrasonographic scan. Lack of bleeding following treatment usually indicates failure; however, prolonged or heavy bleeding is not proof of a complete abortion.

The existence of debris in the uterus (e.g., if seen on ultrasonography) following the treatment procedure will not necessarily require surgery for its removal.

Patients should expect to experience vaginal bleeding or spotting for an average of 9 to 16 days. Women report experiencing heavy bleeding for a median duration of 2 days. Up to 8% of women may experience some type of bleeding for more than 30 days. Persistence of heavy or moderate vaginal bleeding at the time of follow-up, however, could indicate an incomplete abortion.

If complete expulsion has not occurred, but the pregnancy is not ongoing, patients may be treated with another dose of misoprostol 800 mcg buccally. There have been rare reports of uterine rupture in women who took MIFEPREX and misoprostol, including women with prior uterine rupture or uterine scar and women who received multiple doses of misoprostol within 24 hours. Patients who choose to use a repeat dose of misoprostol should have a follow-up visit with their healthcare provider in approximately 7 days to assess for complete termination.

Surgical evacuation is recommended to manage ongoing pregnancies after medical abortion [see Use in Specific Populations (8.1)] . Advise the patient whether you will provide such care or will refer them to another provider as part of counseling prior to prescribing MIFEPREX.

2.4 Contact for Consultation

For consultation 24 hours a day, 7 days a week with an expert in mifepristone, call Danco Laboratories at 1-877-4 Early Option (1-877-432-7596).

3 DOSAGE FORMS AND STRENGTHS

Tablets containing 200 mg of mifepristone each, supplied as 1 tablet on one blister card. MIFEPREX tablets are light yellow, cylindrical, and bi-convex tablets, approximately 11 mm in diameter and imprinted on one side with “MF.”

4 CONTRAINDICATIONS

- Administration of MIFEPREX and misoprostol for the termination of pregnancy (the “treatment procedure”) is contraindicated in patients with any of the following conditions:
  - Confirmed or suspected ectopic pregnancy or undiagnosed adnexal mass (the treatment procedure will not be effective to terminate an ectopic pregnancy) [see Warnings and Precautions (5.4)]
  - Chronic adrenal failure (risk of acute adrenal insufficiency)
  - Concurrent long-term corticosteroid therapy (risk of acute adrenal insufficiency)
  - History of allergy to mifepristone, misoprostol, or other prostaglandins (allergic reactions including anaphylaxis, angioedema, rash, hives, and itching have been reported [see Adverse Reactions (6.2)])
  - Hemorrhagic disorders or concurrent anticoagulant therapy (risk of heavy bleeding)
  - Inherited porphyrias (risk of worsening or of precipitation of attacks)
- Use of MIFEPREX and misoprostol for termination of intrauterine pregnancy is contraindicated in patients with an intrauterine device (“IUD”) in place (the IUD might interfere with pregnancy termination). If the IUD is removed, MIFEPREX may be used.

5 WARNINGS AND PRECAUTIONS

5.1 Infection and Sepsis

As with other types of abortion, cases of serious bacterial infection, including very rare cases of fatal septic shock, have been reported following the use of MIFEPREX [see Boxed Warning] . Healthcare providers evaluating a patient who is undergoing a medical abortion should be alert to the possibility of this rare event. A sustained (> 4 hours) fever of 100.4°F or higher, severe abdominal pain, or pelvic tenderness in the days after a medical abortion may be an indication of infection.

A high index of suspicion is needed to rule out sepsis (e.g., from Clostridium sordellii) if a patient reports abdominal pain or discomfort or general malaise (including weakness, nausea, vomiting, or diarrhea) more than 24 hours after taking misoprostol. Very rarely, deaths have been reported in patients who presented without fever, with or without abdominal pain, but with leukocytosis with a marked left shift, tachycardia, hemoconcentration, and general malaise. No causal relationship between MIFEPREX and misoprostol use and an increased risk of infection or death has been established. Clostridium sordelliiinfections have also been reported very rarely following childbirth (vaginal delivery and caesarian section), and in other gynecologic and non-gynecologic conditions.

5.2 Uterine Bleeding

Uterine bleeding occurs in almost all patients during a medical abortion. Prolonged heavy bleeding (soaking through two thick full-size sanitary pads per hour for two consecutive hours) may be a sign of incomplete abortion or other complications, and prompt medical or surgical intervention may be needed to prevent the development of hypovolemic shock. Counsel patients to seek immediate medical attention if they experience prolonged heavy vaginal bleeding following a medical abortion [see Boxed Warning] .

Women should expect to experience vaginal bleeding or spotting for an average of 9 to 16 days. Women report experiencing heavy bleeding for a median duration of 2 days. Up to 8% of all subjects may experience some type of bleeding for 30 days or more. In general, the duration of bleeding and spotting increased as the duration of the pregnancy increased.

Decreases in hemoglobin concentration, hematocrit, and red blood cell count may occur in patients who bleed heavily.

Excessive uterine bleeding usually requires treatment by uterotonics, vasoconstrictor drugs, surgical uterine evacuation, administration of saline infusions, and/or blood transfusions. Based on data from several large clinical trials, vasoconstrictor drugs were used in 4.3% of all subjects, there was a decrease in hemoglobin of more than 2 g/dL in 5.5% of subjects, and blood transfusions were administered to ≤ 0.1% of subjects. Because heavy bleeding requiring surgical uterine evacuation occurs in about 1% of patients, special care should be given to patients with hemostatic disorders, hypocoagulability, or severe anemia.

5.3 Mifepristone REMS Program

MIFEPREX is available only through a restricted program under a REMS called the Mifepristone REMS Program, because of the risks of serious complications [see Warnings and Precautions (5.1, 5.2)] .

Notable requirements of the Mifepristone REMS Program include the following:

- Prescribers must be certified with the program by completing the Prescriber Agreement Form.
- Patients must sign a Patient Agreement Form.
- MIFEPREX must only be dispensed to patients by or under the supervision of a certified prescriber, or by certified pharmacies on prescriptions issued by certified prescribers.

Further information is available at 1-877-4 Early Option (1-877-432-7596).

5.4 Ectopic Pregnancy

MIFEPREX is contraindicated in patients with a confirmed or suspected ectopic pregnancy because MIFEPREX is not effective for terminating ectopic pregnancies [see Contraindications (4)]. Healthcare providers should remain alert to the possibility that a patient who is undergoing a medical abortion could have an undiagnosed ectopic pregnancy because some of the expected symptoms experienced with a medical abortion (abdominal pain, uterine bleeding) may be similar to those of a ruptured ectopic pregnancy. The presence of an ectopic pregnancy may have been missed even if the patient underwent ultrasonography prior to being prescribed MIFEPREX.

Patients who became pregnant with an IUD in place should be assessed for ectopic pregnancy.

5.5 Rhesus Immunization

The use of MIFEPREX is assumed to require the same preventive measures as those taken prior to and during surgical abortion to prevent rhesus immunization.

6 Adverse Reactions

The following adverse reactions are described in greater detail in other sections:

- Infection and sepsis [see Warnings and Precautions (5.1)]
- Uterine bleeding [see Warnings and Precautions (5.2)]

6.1 Clinical Trials Experience

Because clinical studies are conducted under widely varying conditions, adverse reaction rates observed in the clinical studies of a drug cannot be directly compared to rates in the clinical studies of another drug and may not reflect the rates observed in practice.

Information presented on common adverse reactions relies solely on data from U.S. studies, because rates reported in non-U.S. studies were markedly lower and are not likely generalizable to the U.S. population. In three U.S. clinical studies totaling 1,248 women through 70 days gestation who used mifepristone 200 mg orally followed 24-48 hours later by misoprostol 800 mcg buccally, women reported adverse reactions in diaries and in interviews at the follow-up visit. These studies enrolled generally healthy women of reproductive age without contraindications to mifepristone or misoprostol use according to the MIFEPREX product label. Gestational age was assessed prior to study enrollment using the date of the woman's last menstrual period, clinical evaluation, and/or ultrasound examination.

About 85% of patients report at least one adverse reaction following administration of MIFEPREX and misoprostol, and many can be expected to report more than one such reaction. The most commonly reported adverse reactions (>15%) were nausea, weakness, fever/chills, vomiting, headache, diarrhea, and dizziness (see Table 1). The frequency of adverse reactions varies between studies and may be dependent on many factors, including the patient population and gestational age.

Abdominal pain/cramping is expected in all medical abortion patients and its incidence is not reported in clinical studies. Treatment with MIFEPREX and misoprostol is designed to induce uterine bleeding and cramping to cause termination of an intrauterine pregnancy. Uterine bleeding and cramping are expected consequences of the action of MIFEPREX and misoprostol as used in the treatment procedure. Most patients can expect bleeding more heavily than they do during a heavy menstrual period [see Warnings and Precautions (5.2)] .

Table 1lists the adverse reactions reported in U.S. clinical studies with incidence >15% of women.

Table 1 Adverse Reactions Reported in Women Following Administration of Mifepristone (oral) and Misoprostol (buccal) in U.S. Clinical Studies
Adverse Reaction | # U.S. studies | Number of Evaluable Women | Range of frequency (%) | Upper Gestational Age of Studies Reporting Outcome
Nausea | 3 | 1,248 | 51-75% | 70 days
Weakness | 2 | 630 | 55-58% | 63 days
Fever/chills | 1 | 414 | 48% | 63 days
Vomiting | 3 | 1,248 | 37-48% | 70 days
Headache | 2 | 630 | 41-44% | 63 days
Diarrhea | 3 | 1,248 | 18-43% | 70 days
Dizziness | 2 | 630 | 39-41% | 63 days

One study provided gestational-age stratified adverse reaction rates for women who were 57-63 and 64-70 days; there was little difference in frequency of the reported common adverse reactions by gestational age.

Information on serious adverse reactions was reported in six U.S. and four non-U.S. clinical studies, totaling 30,966 women through 70 days gestation who used mifepristone 200 mg orally followed 24-48 hours later by misoprostol 800 mcg buccally. Serious adverse reaction rates were similar between U.S. and non-U.S. studies, so rates from both U.S. and non-U.S. studies are presented. In the U.S. studies, one studied women through 56 days gestation, four through 63 days gestation, and one through 70 days gestation, while in the non-U.S. studies, two studied women through 63 days gestation, and two through 70 days gestation. Serious adverse reactions were reported in <0.5% of women. Information from the U.S. and non-U.S. studies is presented in Table 2.

Table 2 Serious Adverse Reactions Reported in Women Following Administration of Mifepristone (oral) and Misoprostol (buccal) in U.S. and Non-U.S. Clinical Studies
Adverse Reaction | U.S. |  |  | Non-U.S.
Adverse Reaction | # of studies | Number of Evaluable Women | Range of frequency (%) | # of studies | Number of Evaluable Women | Range of frequency (%)
Transfusion | 4 | 17,774 | 0.03-0.5% | 3 | 12,134 | 0-0.1%
Sepsis | 1 | 629 | 0.2% | 1 | 11,155 | <0.01%*
ER visit | 2 | 1,043 | 2.9-4.6% | 1 | 95 | 0
Hospitalization Related to Medical Abortion | 3 | 14,339 | 0.04-0.6% | 3 | 1,286 | 0-0.7%
Infection without sepsis | 1 | 216 | 0 | 1 | 11,155 | 0.2%
Hemorrhage | NR | NR | NR | 1 | 11,155 | 0.1%
NR= Not reported
* This outcome represents a single patient who experienced death related to sepsis.

6.2 Postmarketing Experience

The following adverse reactions have been identified during postapproval use of MIFEPREX and misoprostol. Because these reactions are reported voluntarily from a population of uncertain size, it is not always possible to reliably estimate their frequency or establish a causal relationship to drug exposure.

Infections and infestations:post-abortal infection (including endometritis, endomyometritis, parametritis, pelvic infection, pelvic inflammatory disease, salpingitis)

Blood and the lymphatic system disorders:anemia

Immune system disorders:allergic reaction (including anaphylaxis, angioedema, hives, rash, itching)

Psychiatric disorders:anxiety

Cardiac disorders:tachycardia (including racing pulse, heart palpitations, heart pounding)

Vascular disorders:syncope, fainting, loss of consciousness, hypotension (including orthostatic), light-headedness

Respiratory, thoracic and mediastinal disorders:shortness of breath

Gastrointestinal disorders:dyspepsia

Musculoskeletal, connective tissue and bone disorders:back pain, leg pain

Reproductive system and breast disorders:uterine rupture, ruptured ectopic pregnancy, hematometra, leukorrhea

General disorders and administration site conditions:pain

7 DRUG INTERACTIONS

7.1 Drugs that May Reduce MIFEPREX Exposure (Effect of CYP 3A4 Inducers on MIFEPREX)

CYP450 3A4 is primarily responsible for the metabolism of mifepristone. CYP3A4 inducers such as rifampin, dexamethasone, St. John's Wort, and certain anticonvulsants (such as phenytoin, phenobarbital, carbamazepine) may induce mifepristone metabolism (lowering serum concentrations of mifepristone). Whether this action has an impact on the efficacy of the dose regimen is unknown. Refer to the follow-up assessment [see Dosage and Administration (2.3)] to verify that treatment has been successful.

7.2 Drugs that May Increase MIFEPREX Exposure (Effect of CYP 3A4 Inhibitors on MIFEPREX)

Although specific drug or food interactions with mifepristone have not been studied, on the basis of this drug's metabolism by CYP 3A4, it is possible that ketoconazole, itraconazole, erythromycin, and grapefruit juice may inhibit its metabolism (increasing serum concentrations of mifepristone). MIFEPREX should be used with caution in patients currently or recently treated with CYP 3A4 inhibitors.

7.3 Effects of MIFEPREX on Other Drugs (Effect of MIFEPREX on CYP 3A4 Substrates)

Based on in vitroinhibition information, coadministration of mifepristone may lead to an increase in serum concentrations of drugs that are CYP 3A4 substrates. Due to the slow elimination of mifepristone from the body, such interaction may be observed for a prolonged period after its administration. Therefore, caution should be exercised when mifepristone is administered with drugs that are CYP 3A4 substrates and have narrow therapeutic range.

8 USE IN SPECIFIC POPULATIONS

8.1 Pregnancy

Risk Summary

MIFEPREX is indicated, in a regimen with misoprostol, for the medical termination of intrauterine pregnancy through 70 days gestation. Risks to pregnant patients are discussed throughout the labeling.

Refer to misoprostol labeling for risks to pregnant patients with the use of misoprostol.

The risk of adverse developmental outcomes with a continued pregnancy after a failed pregnancy termination with MIFEPREX in a regimen with misoprostol is unknown; however, the process of a failed pregnancy termination could disrupt normal embryo-fetal development and result in adverse developmental effects. Birth defects have been reported with a continued pregnancy after a failed pregnancy termination with MIFEPREX in a regimen with misoprostol. In animal reproduction studies, increased fetal losses were observed in mice, rats, and rabbits and skull deformities were observed in rabbits with administration of mifepristone at doses lower than the human exposure level based on body surface area.

Data

Animal Data

In teratology studies in mice, rats and rabbits at doses of 0.25 to 4.0 mg/kg (less than 1/100 to approximately 1/3 the human exposure based on body surface area), because of the antiprogestational activity of mifepristone,fetal losses were much higher than in control animals. Skull deformities were detected in rabbit studies at approximately 1/6 the human exposure, although no teratogenic effects of mifepristone have been observed to date in rats or mice. These deformities were most likely due to the mechanical effects of uterine contractions resulting from inhibition of progesterone action.

8.2 Lactation

MIFEPREX is present in human milk. Limited data demonstrate undetectable to low levels of the drug in human milk with the relative (weight-adjusted) infant dose 0.5% or less as compared to maternal dosing. There is no information on the effects of MIFEPREX in a regimen with misoprostol in a breastfed infant or on milk production. Refer to misoprostol labeling for lactation information with the use of misoprostol. The developmental and health benefits of breast-feeding should be considered along with any potential adverse effects on the breast-fed child from MIFEPREX in a regimen with misoprostol.

8.4 Pediatric Use

Safety and efficacy of MIFEPREX have been established in pregnant females. Data from a clinical study of MIFEPREX that included a subset of 322 females under age 17 demonstrated a safety and efficacy profile similar to that observed in adults.

10 OVERDOSAGE

No serious adverse reactions were reported in tolerance studies in healthy non-pregnant female and healthy male subjects where mifepristone was administered in single doses greater than 1800 mg (ninefold the recommended dose for medical abortion). If a patient ingests a massive overdose, the patient should be observed closely for signs of adrenal failure.

11 DESCRIPTION

MIFEPREX tablets each contain 200 mg of mifepristone, a synthetic steroid with antiprogestational effects. The tablets are light yellow in color, cylindrical, and bi-convex, and are intended for oral administration only. The tablets include the inactive ingredients colloidal silica anhydrous, corn starch, povidone, microcrystalline cellulose, and magnesium stearate.

Mifepristone is a substituted 19-nor steroid compound chemically designated as 11ß-[ p-(Dimethylamino)phenyl]-17ß-hydroxy-17-(1-propynyl)estra-4,9-dien-3-one. Its empirical formula is C29H35NO2. Its structural formula is:

The compound is a yellow powder with a molecular weight of 429.6 and a melting point of 192-196°C. It is very soluble in methanol, chloroform and acetone and poorly soluble in water, hexane and isopropyl ether.

12 CLINICAL PHARMACOLOGY

12.1 Mechanism of Action

The anti-progestational activity of mifepristone results from competitive interaction with progesterone at progesterone-receptor sites. Based on studies with various oral doses in several animal species (mouse, rat, rabbit, and monkey), the compound inhibits the activity of endogenous or exogenous progesterone, resulting in effects on the uterus and cervix that, when combined with misoprostol, result in termination of an intrauterine pregnancy.

During pregnancy, the compound sensitizes the myometrium to the contraction-inducing activity of prostaglandins.

12.2 Pharmacodynamics

Use of MIFEPREX in a regimen with misoprostol disrupts pregnancy by causing decidual necrosis, myometrial contractions, and cervical softening, leading to the expulsion of the products of conception.

Doses of 1 mg/kg or greater of mifepristone have been shown to antagonize the endometrial and myometrial effects of progesterone in women.

Antiglucocorticoid and antiandrogenic activity: Mifepristone also exhibits antiglucocorticoid and weak antiandrogenic activity. The activity of the glucocorticoid dexamethasone in rats was inhibited following doses of 10 to 25 mg/kg of mifepristone. Doses of 4.5 mg/kg or greater in human beings resulted in a compensatory elevation of adrenocorticotropic hormone (ACTH) and cortisol. Antiandrogenic activity was observed in rats following repeated administration of doses from 10 to 100 mg/kg.

12.3 Pharmacokinetics

Mifepristone is rapidly absorbed after oral ingestion with non-linear pharmacokinetics for Cmax after single oral doses of 200 mg and 600 mg in healthy subjects.

Absorption

The absolute bioavailability of a 20 mg mifepristone oral dose in females of childbearing age is 69%. Following oral administration of a single dose of 600 mg, mifepristone is rapidly absorbed, with a peak plasma concentration of 1.98 ± 1.0 mg/L occurring approximately 90 minutes after ingestion.

Following oral administration of a single dose of 200 mg in healthy men (n=8), mean Cmax was 1.77 ± 0.7 mg/L occurring approximately 45 minutes after ingestion. Mean AUC0-∞was 25.8 ± 6.2 mg*hr/L.

Distribution

Mifepristone is 98% bound to plasma proteins, albumin, and α1-acid glycoprotein. Binding to the latter protein is saturable, and the drug displays nonlinear kinetics with respect to plasma concentration and clearance.

Elimination

Following a distribution phase, elimination of mifepristone is slow at first (50% eliminated between 12 and 72 hours) and then becomes more rapid with a terminal elimination half-life of 18 hours.

Metabolism

Metabolism of mifepristone is primarily via pathways involving N-demethylation and terminal hydroxylation of the 17-propynyl chain. In vitrostudies have shown that CYP450 3A4 is primarily responsible for the metabolism. The three major metabolites identified in humans are: (1) RU 42 633, the most widely found in plasma, is the N-monodemethylated metabolite; (2) RU 42 848, which results from the loss of two methyl groups from the 4-dimethylaminophenyl in position 11ß; and (3) RU 42 698, which results from terminal hydroxylation of the 17-propynyl chain.

Excretion

By 11 days after a 600 mg dose of tritiated compound, 83% of the drug has been accounted for by the feces and 9% by the urine. Serum concentrations are undetectable by 11 days.

Specific Populations

The effects of age, hepatic disease and renal disease on the safety, efficacy and pharmacokinetics of mifepristone have not been investigated.

13 NONCLINICAL TOXICOLOGY

13.1 Carcinogenesis, Mutagenesis, Impairment of Fertility

Carcinogenesis

No long-term studies to evaluate the carcinogenic potential of mifepristone have been performed.

Mutagenesis

Results from studies conducted in vitroand in animals have revealed no genotoxic potential for mifepristone. Among the tests carried out were: Ames test with and without metabolic activation; gene conversion test in Saccharomyces cerevisiaeD4 cells; forward mutation in Schizosaccharomyces pompeP1 cells; induction of unscheduled DNA synthesis in cultured HeLa cells; induction of chromosome aberrations in CHO cells; in vitrotest for gene mutation in V79 Chinese hamster lung cells; and micronucleus test in mice.

Impairment of Fertility

In rats, administration of 0.3 mg/kg mifepristone per day caused severe disruption of the estrus cycles for the three weeks of the treatment period. Following resumption of the estrus cycle, animals were mated and no effects on reproductive performance were observed.

14 CLINICAL STUDIES

Safety and efficacy data from clinical studies of mifepristone 200 mg orally followed 24-48 hours later by misoprostol 800 mcg buccally through 70 days gestation are reported below. Success was defined as the complete expulsion of the products of conception without the need for surgical intervention. The overall rates of success and failure, shown by reason for failure based on 22 worldwide clinical studies (including 7 U.S. studies) appear in Table 3.

The demographics of women who participated in the U.S. clinical studies varied depending on study location and represent the racial and ethnic variety of American females. Females of all reproductive ages were represented, including females less than 18 and more than 40 years of age; most were 27 years or younger.

Table 3 Outcome Following Treatment with Mifepristone (oral) and Misoprostol (buccal) Through 70 Days Gestation
 | U.S. Trials | Non-U.S. Trials
N | 16,794 | 18,425
Complete Medical Abortion | 97.4% | 96.2%
Surgical Intervention* | 2.6% | 3.8%
Ongoing Pregnancy** | 0.7% | 0.9%
* Reasons for surgical intervention include ongoing pregnancy, medical necessity, persistent or heavy bleeding after treatment, patient request, or incomplete expulsion.
** Ongoing pregnancy is a subcategory of surgical intervention, indicating the percent of women who have surgical intervention due to an ongoing pregnancy.

The results for clinical studies that reported outcomes, including failure rates for ongoing pregnancy, by gestational age are presented in Table 4.

Table 4 Outcome by Gestational Age Following Treatment with Mifepristone and Misoprostol (buccal) for U.S. and Non-U.S. Clinical Studies
 | <49 days |  |  | 50-56 days |  |  | 57-63 days |  |  | 64-70 days
 | N | % | Number of Evaluable Studies | N | % | Number of Evaluable Studies | N | % | Number of Evaluable Studies | N | % | Number of Evaluable Studies
Complete medical abortion | 12,046 | 98.1 | 10 | 3,941 | 96.8 | 7 | 2,294 | 94.7 | 9 | 479 | 92.7 | 4
Surgical intervention for ongoing pregnancy | 10,272 | 0.3 | 6 | 3,788 | 0.8 | 6 | 2,211 | 2 | 8 | 453 | 3.1 | 3

One clinical study asked subjects through 70 days gestation to estimate when they expelled the pregnancy, with 70% providing data. Of these, 23-38% reported expulsion within 3 hours and over 90% within 24 hours of using misoprostol.

16 HOW SUPPLIED/STORAGE AND HANDLING

is only available through a restricted program called the Mifepristone REMS Program [see Warnings and Precautions (5.3)].

MIFEPREX is supplied as light yellow, cylindrical, and bi-convex tablets imprinted on one side with “MF.” Each tablet contains 200 mg of mifepristone. One tablet is individually blistered on one blister card that is packaged in an individual package (National Drug Code 64875-001-01).

Store at 25°C (77°F); excursions permitted to 15 to 30°C (59 to 86°F) [see USP Controlled Room Temperature].

17 PATIENT COUNSELING INFORMATION

Advise the patient to read the FDA-approved patient labeling (Medication Guide), included with each package of MIFEPREX. Additional copies of the Medication Guide are available by contacting Danco Laboratories at 1-877-4 Early Option (1-877-432-7596) or from www.earlyoptionpill.com.

Serious Infections and Bleeding

- Inform the patient that uterine bleeding and uterine cramping will occur [ see Warnings and Precautions (5.2) ].
- Advise the patient that serious and sometimes fatal infections and bleeding can occur very rarely [ see Warnings and Precautions (5.1, 5.2) ].
- MIFEPREX is only available through a restricted program called the Mifepristone REMS Program [ see Warnings and Precautions (5.3) ]. Under the Mifepristone REMS Program:
  - Patients must sign a Patient Agreement Form.
  - MIFEPREX is only dispensed by or under the supervision of certified prescribers or by certified pharmacies on prescriptions issued by certified prescribers.

Provider Contacts and Actions in Case of Complications

- Ensure that the patient knows whom to call and what to do, including going to an Emergency Room if none of the provided contacts are reachable, or if the patient experiences complications including prolonged heavy bleeding, severe abdominal pain, or sustained fever [see Boxed Warning] .

Compliance with Treatment Schedule and Follow-up Assessment

- Advise the patient that it is necessary to complete the treatment schedule, including a follow-up assessment approximately 7 to14 days after taking MIFEPREX [see Dosage and Administration (2.3)] .
- Explain that
  - prolonged heavy vaginal bleeding is not proof of a complete abortion,
  - if the treatment fails and the pregnancy continues, the risk of fetal malformation is unknown,
  - it is recommended that ongoing pregnancy be managed by surgical termination [see Dosage and Administration (2.3)] . Advise the patient whether you will provide such care or will refer them to another provider.

Subsequent Fertility

- Inform the patient that another pregnancy can occur following medical abortion and before resumption of normal menses.
- Inform the patient that contraception can be initiated as soon as pregnancy expulsion has been confirmed, or before resuming sexual intercourse.

MIFEPREX is a registered trademark of Danco Laboratories, LLC.

Manufactured for:
Danco Laboratories, LLC
P.O. Box 4816
New York, NY 10185
1-877-4 Early Option (1-877-432-7596)
www.earlyoptionpill.com

01/2023

MEDICATION GUIDE
Mifeprex(MIF-eh-prex) (mifepristone tablets, for oral use

Read this information carefully before taking Mifeprex and misoprostol. It will help you understand how the treatment works. This Medication Guide does not take the place of talking with your healthcare provider.

What is the most important information I should know about Mifeprex?
What symptoms should I be concerned with?Although cramping and bleeding are an expected part of ending a pregnancy, rarely, serious and potentially life-threatening bleeding, infections, or other problems can occur following a miscarriage, surgical abortion, medical abortion, or childbirth. Seeking medical attention as soon as possible is needed in these circumstances. Serious infection has resulted in death in a very small number of cases. There is no information that use of Mifeprex and misoprostol caused these deaths. If you have any questions, concerns, or problems, or if you are worried about any side effects or symptoms, you should contact your healthcare provider. You can write down your healthcare provider's telephone number here ________________________.
Be sure to contact your healthcare provider promptly if you have any of the following:

- Heavy Bleeding.Contact your healthcare provider right away if you bleed enough to soak through two thick full-size sanitary pads per hour for two consecutive hours or if you are concerned about heavy bleeding. In about 1 out of 100 women, bleeding can be so heavy that it requires a surgical procedure (surgical aspiration or D&C).
- Abdominal Pain or “Feeling Sick.”If you have abdominal pain or discomfort, or you are “feeling sick,” including weakness, nausea, vomiting, or diarrhea, with or without fever, more than 24 hours after taking misoprostol, you should contact your healthcare provider without delay. These symptoms may be a sign of a serious infection or another problem (including an ectopic pregnancy, a pregnancy outside the womb).
- Fever.In the days after treatment, if you have a fever of 100.4°F or higher that lasts for more than 4 hours, you should contact your healthcare provider right away. Fever may be a symptom of a serious infection or another problem.

If you cannot reach your healthcare provider, go to the nearest hospital emergency room.
What to do if you are still pregnant after Mifeprex with misoprostol treatment.If you are still pregnant, your healthcare provider will talk with you about a surgical procedure to end your pregnancy. In many cases, this surgical procedure can be done in the office/clinic. The chance of birth defects if the pregnancy is not ended is unknown.
Talk with your healthcare provider.Before you take Mifeprex, you should read this Medication Guide and you and your healthcare provider should discuss the benefits and risks of your using Mifeprex.

What is Mifeprex?
Mifeprex is used in a regimen with another prescription medicine called misoprostol, to end an early pregnancy.Early pregnancy means it is 70 days (10 weeks) or less since your last menstrual period began. Mifeprex is not approved for ending pregnancies that are further along. Mifeprex blocks a hormone needed for your pregnancy to continue. When you use Mifeprex on Day 1, you also need to take another medicine called misoprostol 24 to 48 hours after you take Mifeprex, to cause the pregnancy to be passed from your uterus.
The pregnancy is likely to be passed from your uterus within 2 to 24 hours after taking Mifeprex and misoprostol. When the pregnancy is passed from the uterus, you will have bleeding and cramping that will likely be heavier than your usual period. About 2 to 7 out of 100 women taking Mifeprex will need a surgical procedure because the pregnancy did not completely pass from the uterus or to stop bleeding.

Who should not take Mifeprex?
Some patients should not take Mifeprex. Do not take Mifeprex if you:

- Have a pregnancy that is more than 70 days (10 weeks). Your healthcare provider may do a clinical examination, an ultrasound examination, or other testing to determine how far along you are in pregnancy.
- Are using an IUD (intrauterine device or system). It must be taken out before you take Mifeprex.
- Have been told by your healthcare provider that you have a pregnancy outside the uterus (ectopic pregnancy).
- Have problems with your adrenal glands (chronic adrenal failure).
- Take a medicine to thin your blood.
- Have a bleeding problem.
- Have porphyria.
- Take certain steroid medicines.
- Are allergic to mifepristone, misoprostol, or medicines that contain misoprostol, such as Cytotec or Arthrotec.

Ask your healthcare provider if you are not sure about all your medical conditions before taking this medicine to find out if you can take Mifeprex.

What should I tell my healthcare provider before taking Mifeprex?
Before you take Mifeprex, tell your healthcare provider if you:

- cannot follow-up within approximately 7 to 14 days of your first visit
- are breastfeeding. Mifeprex can pass into your breast milk. The effect of the Mifeprex and misoprostol regimen on the breastfed infant or on milk production is unknown.
- are taking medicines, including prescription and over-the-counter medicines, vitamins, and herbal supplements.
  Mifeprex and certain other medicines may affect each other if they are used together. This can cause side effects.

How should I take Mifeprex?
Mifeprex will be given to you by a healthcare provider or pharmacy.
You and your healthcare provider will plan the most appropriate location for you to take the misoprostol, because it may cause bleeding, cramps, nausea, diarrhea, and other symptoms that usually begin within 2 to 24 hours after taking it.
Most women will pass the pregnancy within 2 to 24 hours after taking the misoprostol tablets.

Follow the instruction below on how to take Mifeprex and misoprostol:
Mifeprex (1 tablet) orally + misoprostol (4 tablets) buccally
Day 1:

- Take 1 Mifeprex tablet by mouth.

24 to 48 hours after taking Mifeprex:
Take 4 misoprostol tablets by placing 2 tablets in each cheek pouch (the area between your teeth and cheek - see Figure A) for 30 minutes and then swallow anything left over with a drink of water or another liquid.
The medicines may not work as well if you take misoprostol sooner than 24 hours after Mifeprex or later than 48 hours after Mifeprex.
Misoprostol often causes cramps, nausea, diarrhea, and other symptoms. Your healthcare provider may send you home with medicines for these symptoms.

Figure A(2 tablets between your left cheek and gum and 2 tablets between your right cheek and gum).

Follow-up Assessment at Day 7 to 14:

- This follow-up assessment is very important. You must follow-up with your healthcare provider about 7 to 14 days after you have taken Mifeprex to be sure you are well and that you have had bleeding and the pregnancy has passed from your uterus.
- Your healthcare provider will assess whether your pregnancy has passed from your uterus. If your pregnancy continues, the chance that there may be birth defects is unknown. If you are still pregnant, your healthcare provider will talk with you about a surgical procedure to end your pregnancy.
- If your pregnancy has ended, but has not yet completely passed from your uterus, your provider will talk with you about other choices you have, including waiting, taking another dose of misoprostol, or having a surgical procedure to empty your uterus.

When should I begin birth control?
You can become pregnant again right after your pregnancy ends. If you do not want to become pregnant again, start using birth control as soon as your pregnancy ends or before you start having sexual intercourse again.

What should I avoid while taking Mifeprex and misoprostol?
Do not take any other prescription or over-the-counter medicines (including herbal medicines or supplements) at any time during the treatment period without first asking your healthcare provider about them because they may interfere with the treatment. Ask your healthcare provider about what medicines you can take for pain and other side effects.

What are the possible side effects of Mifeprex and misoprostol?
Mifeprex may cause serious side effects. See “ What is the most important information I should know about Mifeprex?”
Cramping and bleeding.Cramping and vaginal bleeding are expected with this treatment. Usually, these symptoms mean that the treatment is working. But sometimes you can get cramping and bleeding and still be pregnant. This is why you must follow-up with your healthcare provider approximately 7 to 14 days after taking Mifeprex. See “ How should I take Mifeprex?” for more information on your follow-up assessment. If you are not already bleeding after taking Mifeprex, you probably will begin to bleed once you take misoprostol, the medicine you take 24 to 48 hours after Mifeprex. Bleeding or spotting can be expected for an average of 9 to16 days and may last for up to 30 days. Your bleeding may be similar to, or greater than, a normal heavy period. You may see blood clots and tissue. This is an expected part of passing the pregnancy.
The most common side effects of Mifeprex treatment include: nausea, weakness, fever/chills, vomiting, headache, diarrhea and dizziness. Your provider will tell you how to manage any pain or other side effects. These are not all the possible side effects of Mifeprex.
Call your healthcare provider for medical advice about any side effects that bother you or do not go away. You may report side effects to FDA at 1-800-FDA-1088.

General information about the safe and effective use of Mifeprex.
Medicines are sometimes prescribed for purposes other than those listed in a Medication Guide. This Medication Guide summarizes the most important information about Mifeprex. If you would like more information, talk with your healthcare provider. You may ask your healthcare provider for information about Mifeprex that is written for healthcare professionals.
For more information about Mifeprex, go to www.earlyoptionpill.com or call 1-877-4 Early Option (1-877-432-7596).

Manufactured for: Danco Laboratories, LLC
P.O. Box 4816
New York, NY 10185
1-877-4 Early Option (1-877-432-7596) www.earlyoptionpill.com

This Medication Guide has been approved by the U.S. Food and Drug Administration.

Approval 01/2023

Principal Display Panel – 200 mg Carton Label

Mifeprex®

(Mifepristone) Tablets, 200 mg

RX ONLY

NDC: 64875-001-01

1 TABLET

Tablet contains 200 mg Mifepristone.

See package enclosure for full prescribing information.

Dispense the accompanying Medication Guide to each patient

Store at 25°C (77°F); excursions permitted to 15-30°C (59-86°F)
[see USP Controlled Room Temperature].

Protect from light.

Manufactured in Spain for:
Danco Laboratories, LLC
P.O.Box 4816
New York, NY 10185

1-877-4-EARLY OPTION

www.earlyoptionpill.com

DANCO